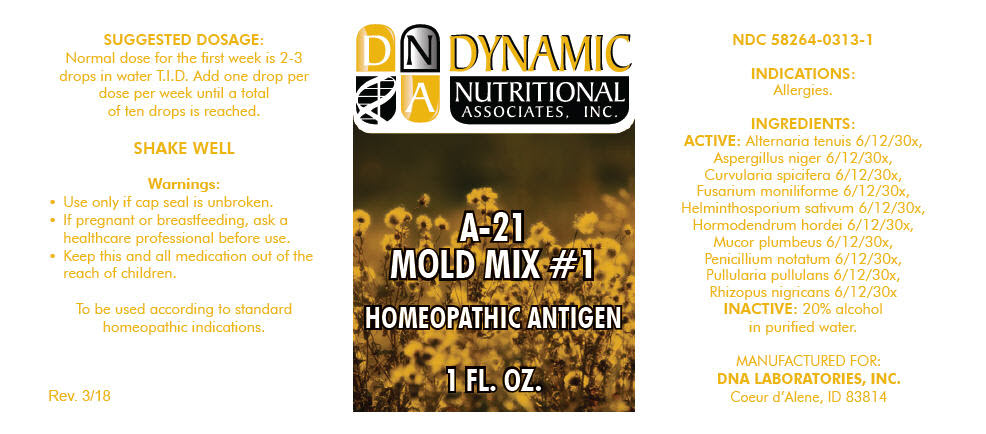 DRUG LABEL: A-21
NDC: 58264-0313 | Form: SOLUTION
Manufacturer: DNA Labs, Inc.
Category: homeopathic | Type: HUMAN OTC DRUG LABEL
Date: 20250109

ACTIVE INGREDIENTS: ALTERNARIA ALTERNATA 30 [hp_X]/1 mL; ASPERGILLUS NIGER VAR. NIGER 30 [hp_X]/1 mL; COCHLIOBOLUS SPICIFER 30 [hp_X]/1 mL; GIBBERELLA FUJIKUROI 30 [hp_X]/1 mL; COCHLIOBOLUS SATIVUS 30 [hp_X]/1 mL; CLADOSPORIUM BRUHNEI 30 [hp_X]/1 mL; MUCOR PLUMBEUS 30 [hp_X]/1 mL; PENICILLIUM CHRYSOGENUM VAR. CHRYSOGENUM 30 [hp_X]/1 mL; AUREOBASIDIUM PULLULANS VAR. PULLUTANS 30 [hp_X]/1 mL; RHIZOPUS STOLONIFER 30 [hp_X]/1 mL
INACTIVE INGREDIENTS: ALCOHOL; WATER

A-21

NDC 58264-0313-1

INDICATIONS

PURPOSE

Allergies.

INGREDIENTS

ACTIVE

Alternaria tenuis 6/12/30x, Aspergillus niger 6/12/30x, Curvularia spicifera 6/12/30x, Fusarium moniliforme 6/12/30x, Helminthosporium sativum 6/12/30x, Hormodendrum hordei 6/12/30x, Mucor plumbeus 6/12/30x, Penicillium notatum 6/12/30x, Pullularia pullulans 6/12/30x, Rhizopus nigricans 6/12/30x

INACTIVE

20% alcohol in purified water.

SUGGESTED DOSAGE

Normal dose for the first week is 2-3 drops in water T.I.D. Add one drop per dose per week until a total of ten drops is reached.

STORAGE AND HANDLING

SHAKE WELL

Warnings

- Use only if cap seal is unbroken.

PREGNANCY OR BREAST FEEDING

- If pregnant or breastfeeding, ask a healthcare professional before use.

KEEP OUT OF REACH OF CHILDREN

- Keep this and all medication out of the reach of children.

To be used according to standard homeopathic indications.

PRINCIPAL DISPLAY PANEL - 1 FL. OZ. Bottle Label

DYNAMIC
NUTRITIONAL
ASSOCIATES, INC.

A-21
MOLD MIX #1

HOMEOPATHIC ANTIGEN

1 FL. OZ.